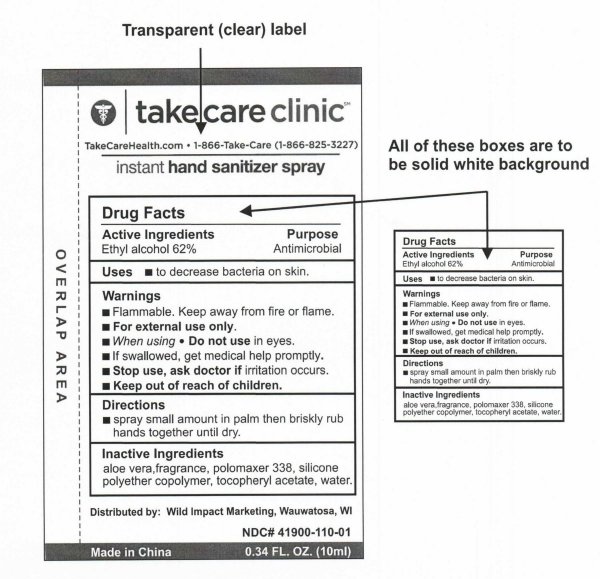 DRUG LABEL: Take Care Clinic Instant Hand Sanitizer Spray
NDC: 41900-110 | Form: SPRAY
Manufacturer: Cinogen Cosmetics Zhaoqing, Ltd.
Category: otc | Type: HUMAN OTC DRUG LABEL
Date: 20091130

ACTIVE INGREDIENTS: ALCOHOL 62 mL/100 mL
INACTIVE INGREDIENTS: ALOE VERA LEAF; ALPHA-TOCOPHEROL; WATER

Take Care Clinic Instant Hand Sanitizer Spray 10ml

PACKAGE LABEL

take care clinic

TakeCareHealth.com 1 866 Take Care (1 866 825 3227)

instant hand sanitizer spray

Distributed by: Wild Impact Marketing, Wauwatosa, WI

NDC number 41900-110-01

Made in China 0.34 FL. Oz. (10ml)

Active Ingredients Purpose

Ethyl Alcohol 62 percent Antimicrobial

Uses

To decrease bacteria on skin.

Warnings

Flammable. Keep away from fire or flame.

For external use only.

When Using

Do not use in eyes.

If swallowed, get medical help promptly.

Stop use, ask doctor if irritation occurs.

Keep out of reach of children.

Directions

Spray small amount in palm then briskly rub hands together until dry.

Inactive Ingredients

aloe vera, fragrance, polomaxer 338, silicone polyether copolymer, tocopheryl acetate , water